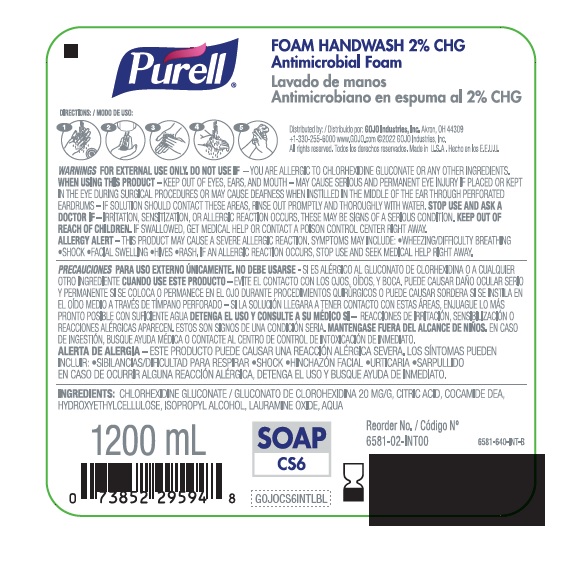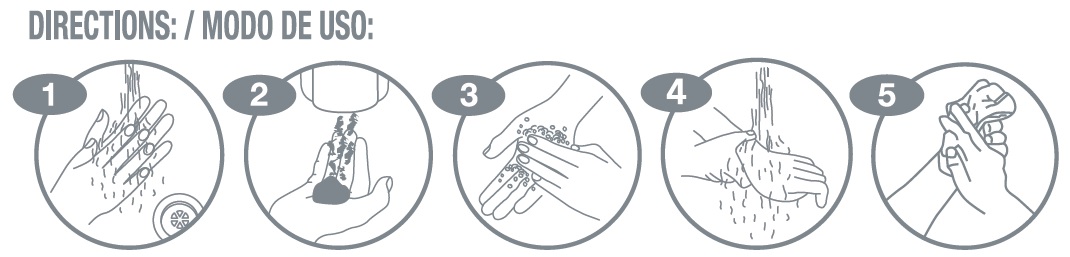 DRUG LABEL: Purell CS Foam Handwash 2% CHG
NDC: 21749-226 | Form: LIQUID
Manufacturer: GOJO Industries, Inc.
Category: otc | Type: HUMAN OTC DRUG LABEL
Date: 20221026

ACTIVE INGREDIENTS: CHLORHEXIDINE GLUCONATE 20 mg/1 mL
INACTIVE INGREDIENTS: CITRIC ACID MONOHYDRATE; HYDROXYETHYL CELLULOSE (2000 CPS AT 1%); ISOPROPYL ALCOHOL; COCO DIETHANOLAMIDE; LAURAMINE OXIDE; WATER

PURELL FOAM HANDWASH 2% CHG Antimicrobial Foam

Uses

Antimicrobial foam handwash

Active Ingredient

Chlorhexidine Gluconate 2%

Purpose

Antiseptic

Warnings

For External Use Only

Do not use

if you are allergic to chlorhexidine gluconate or any other ingredients.

When using this product

keep out of eyes, ears, and mouth. May cause serious and permanent eye injury if placed or kept in the eye during surgical procedures or may cause deafness when instilled in the middle of the ear through perforated eardrums. If solution should contact these areas, rinse out promptly and thoroughly with water.

Stop use and ask a doctor if

Irritation, sensitization, or allergic reaction occurs. These may be signs of a serious condition.

Keep out of reach of children

If swallowed, get medical help or contact a poison control center right away.

Allergy Alert

This product may cause a severe allergic reaction. Symptoms may include:

- wheezing/difficulty breathing
- shock
- facial swelling
- hives
- rash

If an Allergic reaction occurs, stop use and seek medical help right away.

Inactive Ingredients

Citric acid, comide DEA, hydroxyethylcellulose, isopropyl alcohol, lauramine oxide. purified water

PACKAGE LABEL

Foam Handwash 2% CHG

Antimicrobial Foam

Distributed by:

GOJO Industries, Inc.

Akron, OH 44309

+1-330+255-6000

www.GOJO.com

©2022 GOJO Industries, Inc.

All rights reserved.

Made in U.S.A.

1200mL

SOAP

CS6

GOJOCS6INTLBL

6581-640-INT-B